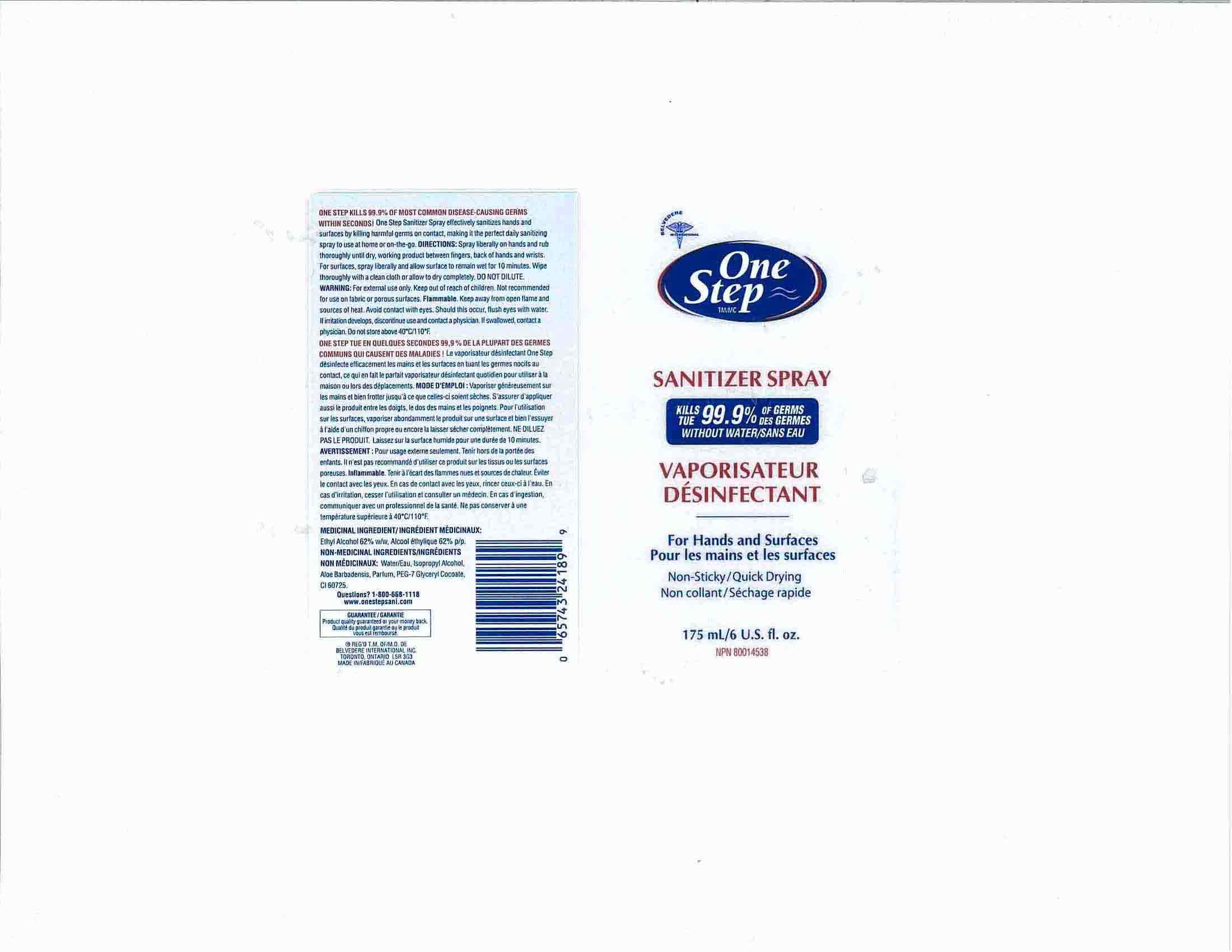 DRUG LABEL: One Step Sanitizer
NDC: 60742-175 | Form: SPRAY
Manufacturer: Belvedere International Inc.
Category: otc | Type: HUMAN OTC DRUG LABEL
Date: 20120209

ACTIVE INGREDIENTS: ALCOHOL 62 mL/100 mL
INACTIVE INGREDIENTS: ALOE VERA LEAF; ISOPROPYL ALCOHOL; PEG-7 GLYCERYL COCOATE

DRUG FACTS

ACTIVE INGREDIENT

ETHYL ALCOHOL 62%

PURPOSE

USE WHENEVER SOAP AND WATER ARE NOT AVAILABLE AND TO SUPPLEMENT ROUTINE HAND WASHING APPLY LIBERALLY TO HAND AND RUB THOROUGHLY UNTIL DRY

KEEP OUT OF REACH OF CHILDREN

INDICATIONS AND USAGE

ONE-STEP-SPRAY-175mL

USE WHENEVER SOAP AND WATER ARE NOT AVAILABLE AND TO SUPPLEMENT ROUTINE HAND WASHING APPLY LIBERALLY TO HAND AND RUB THOROUGHLY UNTIL DRY

WARNINGS

FOR EXTERNAL USE ONLY, KEEP OUT OF REACH OF CHILDREN, NOT RECOMMENDED FOR USE ON FABRIC OR POROUS SURFACES. FLAMMABLE. KEEP AWAY FROM OPEN FLAME AND SOURCE OF HEAT. AVOID CONTACT WITH EYES SHOULD THIS OCCUR FLUSH EYES WITH WATER IF IRRITATION DEVELOPS DISCONTINUE USE AND CONTACT A PHYSICIAN. IF SWALLOWED, CONTACT A PHYSICIAN. DO NOT STORE ABOVE 40 ^0 C/110 ^0F

DOSAGE AND ADMINISTRATION

SPRAY LIBERALLY ON HANDS AND RUB THOROUGHLY UNTIL DRY, WORKING BETWEEN FINGERS, BACK OF HANDS AND WRISTS. FOR SURFACES, SPRAY LIBERALLY AND ALLOW SURFACE TO REMAIN WET FOR 10 MINUTES, WIPE THOROUGHLY WITH A CLEAN CLOTH OR ALLOW TO DRY COMPLETELY. DO NOT DILUTE.

INACTIVE INGREDIENT

WATER, ISOPROPYL ALCOHOL, ALOE BARBADENSIS, PARFUM, PEG-7 GLYCERYL COCOATE, CI 60725

PACKAGE LABEL

ONE-STEP-SPRAY-175mL.jpg